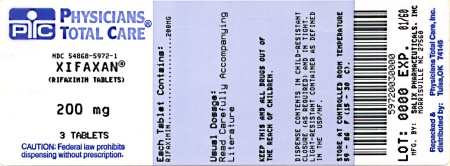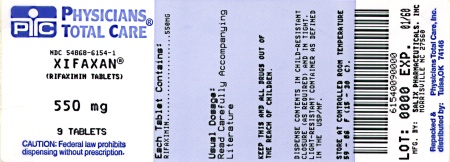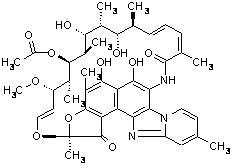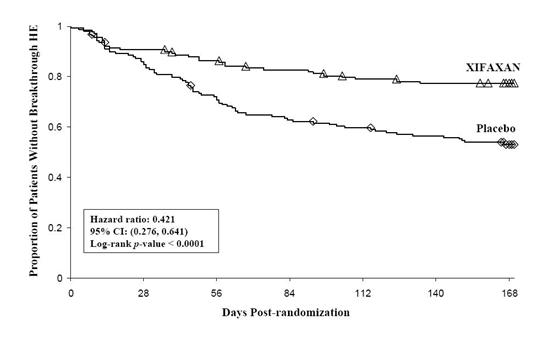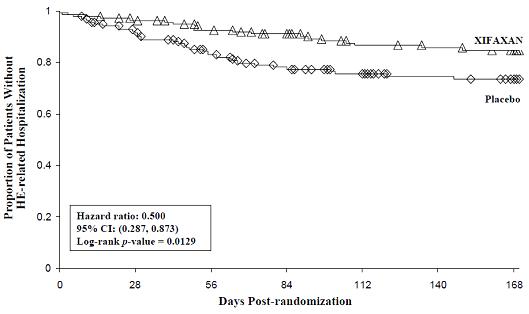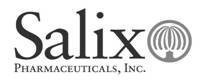 DRUG LABEL: XIFAXAN
NDC: 54868-5972 | Form: TABLET
Manufacturer: Physicians Total Care, Inc.
Category: prescription | Type: HUMAN PRESCRIPTION DRUG LABEL
Date: 20111228

ACTIVE INGREDIENTS: RIFAXIMIN 200 mg/1 1
INACTIVE INGREDIENTS: SILICON DIOXIDE; EDETATE DISODIUM; GLYCERYL PALMITOSTEARATE; HYPROMELLOSES; CELLULOSE, MICROCRYSTALLINE; PROPYLENE GLYCOL; FERRIC OXIDE RED; SODIUM STARCH GLYCOLATE TYPE A POTATO; TALC; TITANIUM DIOXIDE

HIGHLIGHTS OF PRESCRIBING INFORMATION

These highlights do not include all the information needed to use XIFAXAN safely and effectively. See full prescribing information for XIFAXAN.
XIFAXAN® (rifaximin) Tablets
Initial U.S. Approval: 2004
To reduce the development of drug-resistant bacteria and maintain the effectiveness of XIFAXAN and other antibacterial drugs, XIFAXAN should be used only to treat or prevent infections that are proven or strongly suspected to be caused by bacteria.

1 INDICATIONS AND USAGE

XIFAXAN is a rifamycin antibacterial indicated for:

- The treatment of patients (≥ 12 years of age) with travelers’ diarrhea (TD) caused by noninvasive strains of Escherichia coli (1.1)
- Reduction in risk of overt hepatic encephalopathy (HE) recurrence in patients ≥ 18 years of age (1.2)

Limitations of Use

- TD: Do not use in patients with diarrhea complicated by fever or blood in the stool or diarrhea due to pathogens other than Escherichia coli (1.1)

2 DOSAGE AND ADMINISTRATION

- Travelers’ diarrhea: One 200 mg tablet taken orally three times a day for 3 days, with or without food (2.1)
- Hepatic encephalopathy: One 550 mg tablet taken orally two times a day, with or without food (2.2)

3 DOSAGE FORMS AND STRENGTHS

- 200 mg and 550 mg tablets (3)

4 CONTRAINDICATIONS

History of hypersensitivity to rifaximin, rifamycin antimicrobial agents, or any of the components of XIFAXAN (4.1)

5 WARNINGS AND PRECAUTIONS

- Travelers’ Diarrhea Not Caused by E. coli: XIFAXAN was not effective in diarrhea complicated by fever and/or blood in the stool or diarrhea due to pathogens other than E. coli. If diarrhea symptoms get worse or persist for more than 24-48 hours, discontinue XIFAXAN and consider alternative antibiotics (5.1)
- Clostridium difficile-Associated Diarrhea: Evaluate if diarrhea occurs after therapy or does not improve or worsens during therapy (5.2)
- Hepatic Impairment: Use with caution in patients with severe (Child-Pugh C) hepatic impairment (5.4, 8.7)

6 ADVERSE REACTIONS

- Most common adverse reactions in travelers’ diarrhea (≥ 5%): Flatulence, headache, abdominal pain, rectal tenesmus, defecation urgency and nausea (6.1)
- Most common adverse reactions in HE (≥ 10%): Peripheral edema, nausea, dizziness, fatigue, ascites, flatulence, and headache (6.1)

To report suspected adverse reactions, contact Salix Pharmaceuticals at 1-800-508-0024 and www.Salix.com or FDA at 1-800-FDA-1088 or www.fda.gov/medwatch

8 USE IN SPECIFIC POPULATIONS

- Pregnancy: Based on animal data, may cause fetal harm (8.1)
- Nursing Mothers: Discontinue nursing or drug, taking into account the importance of the drug to the mother (8.3)

FULL PRESCRIBING INFORMATION

1 INDICATIONS AND USAGE

To reduce the development of drug-resistant bacteria and maintain the effectiveness of XIFAXAN and other antibacterial drugs, XIFAXAN when used to treat infection should be used only to treat or prevent infections that are proven or strongly suspected to be caused by susceptible bacteria. When culture and susceptibility information are available, they should be considered in selecting or modifying antibacterial therapy. In the absence of such data, local epidemiology and susceptibility patterns may contribute to the empiric selection of therapy.

1.1 Travelers’ Diarrhea

XIFAXAN 200 mg is indicated for the treatment of patients (≥ 12 years of age) with travelers’ diarrhea caused by noninvasive strains of Escherichia coli [see Warnings and Precautions (5), Clinical Pharmacology (12.4) and Clinical Studies (14.1)].

Limitations of Use

XIFAXAN should not be used in patients with diarrhea complicated by fever or blood in the stool or diarrhea due to pathogens other than Escherichia coli.

1.2 Hepatic Encephalopathy

XIFAXAN 550 mg is indicated for reduction in risk of overt hepatic encephalopathy (HE) recurrence in patients ≥ 18 years of age.

In the trials of XIFAXAN for HE, 91% of the patients were using lactulose concomitantly. Differences in the treatment effect of those patients not using lactulose concomitantly could not be assessed.

XIFAXAN has not been studied in patients with MELD (Model for End-Stage Liver Disease) scores > 25, and only 8.6% of patients in the controlled trial had MELD scores over 19. There is increased systemic exposure in patients with more severe hepatic dysfunction [see Warnings and Precautions (5.4), Use in Specific Populations (8.7), Clinical Pharmacology (12.3)].

2 DOSAGE AND ADMINISTRATION

2.1 Dosage for Travelers’ Diarrhea

The recommended dose of XIFAXAN is one 200 mg tablet taken orally three times a day for 3 days. XIFAXAN can be administered orally, with or without food [see Clinical Pharmacology (12.3)].

2.2 Dosage for Hepatic Encephalopathy

The recommended dose of XIFAXAN is one 550 mg tablet taken orally two times a day, with or without food[see Clinical Pharmacology (12.3)].

3 DOSAGE FORMS AND STRENGTHS

XIFAXAN is a pink-colored biconvex tablet and is available in the following strengths:

- 200 mg – a round tablet debossed with “Sx” on one side.
- 550 mg – an oval tablet debossed with “rfx” on one side.

4 CONTRAINDICATIONS

4.1 Hypersensitivity

XIFAXAN is contraindicated in patients with a hypersensitivity to rifaximin, any of the rifamycin antimicrobial agents, or any of the components in XIFAXAN. Hypersensitivity reactions have included exfoliative dermatitis, angioneurotic edema, and anaphylaxis [see Adverse Reactions (6.2)].

5 WARNINGS AND PRECAUTIONS

5.1 Travelers’ Diarrhea Not Caused by Escherichia coli

XIFAXAN was not found to be effective in patients with diarrhea complicated by fever and/or blood in the stool or diarrhea due to pathogens other than Escherichia coli.

Discontinue XIFAXAN if diarrhea symptoms get worse or persist more than 24-48 hours and alternative antibiotic therapy should be considered.

XIFAXAN is not effective in cases of travelers’ diarrhea due to Campylobacter jejuni. The effectiveness of XIFAXAN in travelers’ diarrhea caused by Shigella spp. and Salmonella spp. has not been proven. XIFAXAN should not be used in patients where Campylobacter jejuni, Shigella spp., or Salmonella spp. may be suspected as causative pathogens.

5.2 Clostridium difficile-Associated Diarrhea

Clostridium difficile-associated diarrhea (CDAD) has been reported with use of nearly all antibacterial agents, including XIFAXAN, and may range in severity from mild diarrhea to fatal colitis. Treatment with antibacterial agents alters the normal flora of the colon which may lead to overgrowth of C. difficile.

C. difficile produces toxins A and B which contribute to the development of CDAD. Hypertoxin producing strains of C. difficile cause increased morbidity and mortality, as these infections can be refractory to antimicrobial therapy and may require colectomy. CDAD must be considered in all patients who present with diarrhea following antibiotic use. Careful medical history is necessary since CDAD has been reported to occur over two months after the administration of antibacterial agents.

If CDAD is suspected or confirmed, ongoing antibiotic use not directed against C. difficile may need to be discontinued. Appropriate fluid and electrolyte management, protein supplementation, antibiotic treatment of C. difficile, and surgical evaluation should be instituted as clinically indicated.

5.3 Development of Drug Resistant Bacteria

Prescribing XIFAXAN for travelers’ diarrhea in the absence of a proven or strongly suspected bacterial infection or a prophylactic indication is unlikely to provide benefit to the patient and increases the risk of the development of drug-resistant bacteria.

5.4 Severe (Child-Pugh C) Hepatic Impairment

There is increased systemic exposure in patients with severe hepatic impairment. Animal toxicity studies did not achieve systemic exposures that were seen in patients with severe hepatic impairment. The clinical trials were limited to patients with MELD scores <25. Therefore, caution should be exercised when administering XIFAXAN to patients with severe hepatic impairment (Child-Pugh C)

[see Use in Specific Populations (8.7), Nonclinical Toxicology (13.2) and Clinical Studies (14.2)].

6 ADVERSE REACTIONS

6.1 Clinical Studies Experience

Because clinical trials are conducted under widely varying conditions, adverse reaction rates observed in the clinical trials of a drug cannot be directly compared to rates in the clinical trials of another drug and may not reflect the rates observed in practice.

Travelers’ Diarrhea

The safety of XIFAXAN 200 mg taken three times a day was evaluated in patients with travelers’ diarrhea consisting of 320 patients in two placebo-controlled clinical trials with 95% of patients receiving three or four days of treatment with XIFAXAN. The population studied had a mean age of 31.3 (18-79) years of which approximately 3% were ≥ 65 years old, 53% were male and 84% were White, 11% were Hispanic.

Discontinuations due to adverse reactions occurred in 0.4% of patients. The adverse reactions leading to discontinuation were taste loss, dysentery, weight decrease, anorexia, nausea and nasal passage irritation.

All adverse reactions for XIFAXAN 200 mg three times daily that occurred at a frequency ≥ 2% in the two placebo-controlled trials combined are provided in Table 1. (These include adverse reactions that may be attributable to the underlying disease.)

Table 1. All Adverse Reactions With an Incidence ≥2% Among Patients Receiving XIFAXAN Tablets, 200 mg Three Times Daily, in Placebo-Controlled Studies
MedDRA Preferred Term | Number (%) of Patients
MedDRA Preferred Term | XIFAXAN Tablets, 600 mg/day (N = 320) | Placebo N = 228
Flatulence | 36 (11%) | 45 (20%)
Headache | 31 (10%) | 21 (9%)
Abdominal Pain NOS* | 23 (7%) | 23 (10%)
Rectal Tenesmus | 23 (7%) | 20 (9%)
Defecation Urgency | 19 (6%) | 21 (9%)
Nausea | 17 (5%) | 19 (8%)
Constipation | 12 (4%) | 8 (4%)
Pyrexia | 10 (3%) | 10 (4%)
Vomiting NOS | 7 (2%) | 4 (2%)
*NOS: Not otherwise specified

The following adverse reactions, presented by body system, have also been reported in <2% of patients taking XIFAXAN in the two placebo-controlled clinical trials where the 200 mg tablet was taken three times a day for travelers’ diarrhea. The following includes adverse reactions regardless of causal relationship to drug exposure.

Blood and Lymphatic System Disorders: Lymphocytosis, monocytosis, neutropenia

Ear and Labyrinth Disorders: Ear pain, motion sickness, tinnitus

Gastrointestinal Disorders: Abdominal distension, diarrhea NOS, dry throat, fecal abnormality NOS, gingival disorder NOS, inguinal hernia NOS, dry lips, stomach discomfort

General Disorders and Administration Site Conditions: Chest pain, fatigue, malaise, pain NOS, weakness

Infections and Infestations: Dysentery NOS, respiratory tract infection NOS, upper respiratory tract infection NOS

Injury and Poisoning: Sunburn

Investigations: Aspartate aminotransferase increased, blood in stool, blood in urine, weight decreased

Metabolic and Nutritional Disorders: Anorexia, dehydration

Musculoskeletal, Connective Tissue, and Bone Disorders: Arthralgia, muscle spasms, myalgia, neck pain

Nervous System Disorders: Abnormal dreams, dizziness, migraine NOS, syncope, loss of taste

Psychiatric Disorders: Insomnia

Renal and Urinary Disorders: Choluria, dysuria, hematuria, polyuria, proteinuria, urinary frequency

Respiratory, Thoracic, and Mediastinal Disorders: Dyspnea NOS, nasal passage irritation, nasopharyngitis, pharyngitis, pharyngolaryngeal pain, rhinitis NOS, rhinorrhea

Skin and Subcutaneous Tissue Disorders: Clamminess, rash NOS, sweating increased

Vascular Disorders: Hot flashes NOS

Hepatic Encephalopathy

The data described below reflect exposure to XIFAXAN 550 mg in 348 patients, including 265 exposed for 6 months and 202 exposed for more than a year (mean exposure was 364 days). The safety of XIFAXAN 550 mg taken two times a day for reducing the risk of overt hepatic encephalopathy recurrence in adult patients was evaluated in a 6-month placebo-controlled clinical trial (n = 140) and in a long term follow-up study (n = 280). The population studied had a mean age of 56.26 (range: 21-82) years; approximately 20% of the patients were ≥ 65 years old, 61% were male, 86% were White, and 4% were Black. Ninety-one percent of patients in the trial were taking lactulose concomitantly. All adverse reactions that occurred at an incidence ≥ 5% and at a higher incidence in XIFAXAN 550 mg-treated subjects than in the placebo group in the 6-month trial are provided in Table 2. (These include adverse events that may be attributable to the underlying disease).

Table 2: Adverse Reactions Occurring in ≥ 5% of Patients Receiving XIFAXAN and at a Higher Incidence Than Placebo
 | Number (%) of Patients
MedDRA Preferred Term | XIFAXAN Tablets 550 mg TWICE DAILY N = 140 | Placebo N = 159
MedDRA Preferred Term | Edema peripheral | 21 (15%) | 13 (8%)
Nausea | 20 (14%) | 21 (13%)
Dizziness | 18 (13%) | 13 (8%)
Fatigue | 17 (12%) | 18 (11%)
Ascites | 16 (11%) | 15 (9%)
Muscle spasms | 13 (9%) | 11 (7%)
Pruritus | 13 (9%) | 10 (6%)
Abdominal pain | 12 (9%) | 13 (8%)
Abdominal distension | 11 (8%) | 12 (8%)
Anemia | 11 (8%) | 6 (4%)
Cough | 10 (7%) | 11 (7%)
Depression | 10 (7%) | 8 (5%)
Insomnia | 10 (7%) | 11 (7%)
Nasopharyngitis | 10 (7%) | 10 (6%)
Abdominal pain upper | 9 (6%) | 8 (5%)
Arthralgia | 9 (6%) | 4 (3%)
Back pain | 9 (6%) | 10 (6%)
Constipation | 9 (6%) | 10 (6%)
Dyspnea | 9 (6%) | 7 (4%)
Pyrexia | 9 (6%) | 5 (3%)
Rash | 7 (5%) | 6 (4%)

The following adverse reactions, presented by body system, have also been reported in the placebo-controlled clinical trial in greater than 2% but less than 5% of patients taking XIFAXAN 550 mg taken orally two times a day for hepatic encephalopathy. The following includes adverse events occurring at a greater incidence than placebo, regardless of causal relationship to drug exposure.

Ear and Labyrinth Disorders: Vertigo

Gastrointestinal Disorders: Abdominal pain lower, abdominal tenderness, dry mouth, esophageal variceal bleed, stomach discomfort

General Disorders and Administration Site Conditions: Chest pain, generalized edema, influenza like illness, pain NOS

Infections and Infestations: Cellulitis, pneumonia, rhinitis, upper respiratory tract infection NOS

Injury, Poisoning and Procedural Complications: Contusion, fall, procedural pain

Investigations: Weight increased

Metabolic and Nutritional Disorders: Anorexia, dehydration, hyperglycemia, hyperkalemia, hypoglycemia, hyponatremia

Musculoskeletal, Connective Tissue, and Bone Disorders: Myalgia, pain in extremity

Nervous System Disorders: Amnesia, disturbance in attention, hypoesthesia, memory impairment, tremor

Psychiatric Disorders: Confusional state

Respiratory, Thoracic, and Mediastinal Disorders: Epistaxis

Vascular Disorders: Hypotension

6.2 Postmarketing Experience

The following adverse reactions have been identified during post approval use of XIFAXAN. Because these reactions are reported voluntarily from a population of unknown size, estimates of frequency cannot be made. These reactions have been chosen for inclusion due to either their seriousness, frequency of reporting or causal connection to XIFAXAN.

Infections and Infestations

Cases of C. difficile-associated colitis have been reported [see Warnings and Precautions (5.2)].

General

Hypersensitivity reactions, including exfoliative dermatitis, rash, angioneurotic edema (swelling of face and tongue and difficulty swallowing), urticaria, flushing, pruritus and anaphylaxis have been reported. These events occurred as early as within 15 minutes of drug administration.

7 DRUG INTERACTIONS

In vitro studies have shown that rifaximin did not inhibit cytochrome P450 isoenzymes 1A2, 2A6, 2B6, 2C9, 2C19, 2D6, 2E1 and CYP3A4 at concentrations ranging from 2 to 200 ng/mL [see Clinical Pharmacology (12.3)]. Rifaximin is not expected to inhibit these enzymes in clinical use.

An in vitro study has suggested that rifaximin induces CYP3A4 [see Clinical Pharmacology (12.3)]. However, in patients with normal liver function, rifaximin at the recommended dosing regimen is not expected to induce CYP3A4. It is unknown whether rifaximin can have a significant effect on the pharmacokinetics of concomitant CYP3A4 substrates in patients with reduced liver function who have elevated rifaximin concentrations.

An in vitro study suggested that rifaximin is a substrate of P-glycoprotein. It is unknown whether concomitant drugs that inhibit P-glycoprotein can increase the systemic exposure of rifaximin [see Clinical Pharmacology (12.3)].

8 USE IN SPECIFIC POPULATIONS

8.1 Pregnancy

Pregnancy Category C

There are no adequate and well controlled studies in pregnant women. Rifaximin has been shown to be teratogenic in rats and rabbits at doses that caused maternal toxicity. XIFAXAN tablets should be used during pregnancy only if the potential benefit justifies the potential risk to the fetus.

Administration of rifaximin to pregnant rats and rabbits at dose levels that caused reduced body weight gain resulted in eye malformations in both rat and rabbit fetuses. Additional malformations were observed in fetal rabbits that included cleft palate, lumbar scoliosis, brachygnathia, interventricular septal defect, and large atrium.

The fetal rat malformations were observed in a study of pregnant rats administered a high dose that resulted in 16 times the therapeutic dose to diarrheic patients or 1 times the therapeutic dose to patients with hepatic encephalopathy (based upon plasma AUC comparisons). Fetal rabbit malformations were observed from pregnant rabbits administered mid and high doses that resulted in 1 or 2 times the therapeutic dose to diarrheic patients or less than 0.1 times the dose in patients with hepatic encephalopathy, based upon plasma AUC comparisons.

Post-natal developmental effects were not observed in rat pups from pregnant/lactating female rats dosed during the period from gestation to Day 20 post-partum at the highest dose which resulted in approximately 16 times the human therapeutic dose for travelers’ diarrhea (based upon AUCs) or approximately 1 times the AUCs derived from therapeutic doses to patients with hepatic encephalopathy.

8.3 Nursing Mothers

It is not known whether rifaximin is excreted in human milk. Because many drugs are excreted in human milk and because of the potential for adverse reactions in nursing infants from XIFAXAN, a decision should be made whether to discontinue nursing or to discontinue the drug, taking into account the importance of the drug to the mother.

8.4 Pediatric Use

The safety and effectiveness of XIFAXAN 200 mg in pediatric patients with travelers’ diarrhea less than 12 years of age have not been established.

The safety and effectiveness of XIFAXAN 550 mg for HE have not been established in patients < 18 years of age.

8.5 Geriatric Use

Clinical studies with rifaximin 200 mg for travelers’ diarrhea did not include sufficient numbers of patients aged 65 and over to determine whether they respond differently than younger subjects.

In the controlled trial with XIFAXAN 550 mg for hepatic encephalopathy, 19.4% were 65 and over, while 2.3% were 75 and over. No overall differences in safety or effectiveness were observed between these subjects and younger subjects, and other reported clinical experience has not identified differences in responses between the elderly and younger patients, but greater sensitivity of some older individuals cannot be ruled out.

8.6 Renal Impairment

The pharmacokinetics of rifaximin in patients with impaired renal function has not been studied.

8.7 Hepatic Impairment

Following administration of XIFAXAN 550 mg twice daily to patients with a history of hepatic encephalopathy, the systemic exposure (i.e., AUCτ) of rifaximin was about 10-, 13-, and 20-fold higher in those patients with mild (Child-Pugh A), moderate (Child-Pugh B) and severe (Child-Pugh C) hepatic impairment, respectively, compared to that in healthy volunteers. No dosage adjustment is recommended because rifaximin is presumably acting locally. Nonetheless, caution should be exercised when XIFAXAN is administered to patients with severe hepatic impairment

[see Warnings and Precautions (5.4), Clinical Pharmacology (12.3), Nonclinical Toxicology (13.2), and Clinical Studies (14.2)].

10 OVERDOSAGE

No specific information is available on the treatment of overdosage with XIFAXAN. In clinical studies at doses higher than the recommended dose (> 600 mg/day for travelers’ diarrhea or > 1100 mg/day for hepatic encephalopathy), adverse reactions were similar in subjects who received doses higher than the recommended dose and placebo. In the case of overdosage, discontinue XIFAXAN, treat symptomatically, and institute supportive measures as required.

11 DESCRIPTION

XIFAXAN tablets contain rifaximin, a non-aminoglycoside semi-synthetic, nonsystemic antibiotic derived from rifamycin SV. Rifaximin is a structural analog of rifampin. The chemical name for rifaximin is (2S,16Z,18E,20S,21S,22R,23R,24R,25S,26S,27S,28E)-5,6,21,23,25-pentahydroxy-27-methoxy-2,4,11,16,20,22,24,26-octamethyl-2,7-(epoxypentadeca-[1,11,13]trienimino)benzofuro[4,5-e]pyrido[1,2-á]-benzimidazole-1,15(2H)-dione,25-acetate. The empirical formula is C43H51N3O11 and its molecular weight is 785.9. The chemical structure is represented below:

XIFAXAN Tablets for oral administration are film-coated and contain 200 mg or 550 mg of rifaximin.

Inactive ingredients:

Each 200 mg tablet contains colloidal silicon dioxide, disodium edetate, glycerol palmitostearate, hypromellose, microcrystalline cellulose, propylene glycol, red iron oxide, sodium starch glycolate, talc, and titanium dioxide.

Each 550 mg tablet contains colloidal silicon dioxide, glycerol palmitostearate, microcrystalline cellulose, polyethylene glycol/macrogol, polyvinyl alcohol, red iron oxide, sodium starch glycolate, talc, and titanium dioxide.

12 CLINICAL PHARMACOLOGY

12.1 Mechanism of Action

Rifaximin is an antibacterial drug [see Clinical Pharmacology (12.4)].

12.3 Pharmacokinetics

Absorption

Travelers’ Diarrhea

Systemic absorption of rifaximin (200 mg three times daily) was evaluated in 13 subjects challenged with shigellosis on Days 1 and 3 of a three-day course of treatment. Rifaximin plasma concentrations and exposures were low and variable. There was no evidence of accumulation of rifaximin following repeated administration for 3 days (9 doses). Peak plasma rifaximin concentrations after 3 and 9 consecutive doses ranged from 0.81 to 3.4 ng/mL on Day 1 and 0.68 to 2.26 ng/mL on Day 3. Similarly, AUC0-last estimates were 6.95 ± 5.15 ng•h/mL on Day 1 and 7.83 ± 4.94 ng•h/mL on Day 3. XIFAXAN is not suitable for treating systemic bacterial infections because of limited systemic exposure after oral administration [see Warnings and Precautions (5.1)].

Hepatic Encephalopathy

After a single dose and multiple doses of rifaximin 550 mg in healthy subjects, the mean time to reach peak plasma concentrations was about an hour. The pharmacokinetic (PK) parameters were highly variable and the accumulation ratio based on AUC was 1.37.

The PK of rifaximin in patients with a history of HE was evaluated after administration of XIFAXAN, 550 mg two times a day. The PK parameters were associated with a high variability and mean rifaximin exposure (AUCτ) in patients with a history of HE (147 ng•h/mL) was approximately 12-fold higher than that observed in healthy subjects following the same dosing regimen (12.3 ng•h/mL). When PK parameters were analyzed based on Child-Pugh Class A, B, and C, the mean AUCτ was 10-, 13-, and 20-fold higher, respectively, compared to that in healthy subjects (Table 3).

Table 3. Mean (± SD) Pharmacokinetic Parameters of Rifaximin at Steady-State in Patients with a History of Hepatic Encephalopathy by Child-Pugh Class^1
 | Healthy Subjects (n = 14) | Child-Pugh Class
 | Healthy Subjects (n = 14) | A (n = 18) | B (n = 7) | C (n = 4)
AUCtau; (ng•h/mL) | 12.3 ± 4.8 | 118 ± 67.8 | 161 ± 101 | 246 ± 120
Cmax; (ng/mL) | 3.4 ± 1.6 | 19.5 ± 11.4 | 25.1 ± 12.6 | 35.5 ± 12.5
Tmax^2; (h) | 0.8 (0.5, 4.0) | 1 (0.9, 10) | 1 (0.97, 1) | 1 (0, 2)
^1Cross-study comparison with PK parameters in healthy subjects
^2Median (range)

Food Effect in Healthy Subjects

A high-fat meal consumed 30 minutes prior to XIFAXAN dosing in healthy subjects delayed the mean time to peak plasma concentration from 0.75 to 1.5 hours and increased the systemic exposure (AUC) of rifaximin by 2-fold (Table 4).

Table 4. Mean (± SD) Pharmacokinetic Parameters After Single-Dose Administration of XIFAXAN Tablets 550 mg in Healthy Subjects Under Fasting and Fed Conditions (N = 12)
Parameter | Fasting | Fed
Cmax (ng/mL) | 4.1 ± 1.5 | 4.8 ± 4.3
Tmax^1 (h) | 0.8 (0.5, 2.1) | 1.5 (0.5, 4.1)
Half-Life (h) | 1.8 ± 1.4 | 4.8 ± 1.3
AUC (ng•h/mL) | 11.1 ± 4.2 | 22.5 ± 12
^1 Median (range)

XIFAXAN can be administered with or without food [see Dosage and Administration (2.1 and 2.2)].

Distribution

Rifaximin is moderately bound to human plasma proteins. In vivo, the mean protein binding ratio was 67.5% in healthy subjects and 62% in patients with hepatic impairment when XIFAXAN 550 mg was administered.

Metabolism and Excretion

In a mass balance study, after administration of 400 mg ^14C-rifaximin orally to healthy volunteers, of the 96.94% total recovery, 96.62% of the administered radioactivity was recovered in feces almost exclusively as the unchanged drug and 0.32% was recovered in urine mostly as metabolites with 0.03% as the unchanged drug. Rifaximin accounted for 18% of radioactivity in plasma. This suggests that the absorbed rifaximin undergoes metabolism with minimal renal excretion of the unchanged drug. The enzymes responsible for metabolizing rifaximin are unknown.

In a separate study, rifaximin was detected in the bile after cholecystectomy in patients with intact gastrointestinal mucosa, suggesting biliary excretion of rifaximin.

Specific Populations

Hepatic Impairment

The systemic exposure of rifaximin was markedly elevated in patients with hepatic impairment compared to healthy subjects. The mean AUC in patients with Child-Pugh Class C hepatic impairment was 2-fold higher than in patients with Child-Pugh Class A hepatic impairment (see Table 3), [see Warnings and Precautions (5.4) and Use in Specific Populations (8.7)].

Renal Impairment

The pharmacokinetics of rifaximin in patients with impaired renal function has not been studied.

Drug Interactions

In vitro drug interaction studies have shown that rifaximin, at concentrations ranging from 2 to 200 ng/mL, did not inhibit human hepatic cytochrome P450 isoenzymes 1A2, 2A6, 2B6, 2C9, 2C19, 2D6, 2E1, and 3A4.

In an in vitro study, rifaximin was shown to induce CYP3A4 at the concentration of 0.2 µM.

An in vitro study suggests that rifaximin is a substrate of P-glycoprotein. In the presence of P-glycoprotein inhibitor verapamil, the efflux ratio of rifaximin was reduced greater than 50% in vitro. The effect of P-glycoprotein inhibition on rifaximin was not evaluated in vivo.

The inhibitory effect of rifaximin on P-gp transporter was observed in an in vitro study. The effect of rifaximin on P-gp transporter was not evaluated in vivo.

Midazolam

The effect of rifaximin 200 mg administered orally every 8 hours for 3 days and for 7 days on the pharmacokinetics of a single dose of either midazolam 2 mg intravenous or midazolam 6 mg orally was evaluated in healthy subjects. No significant difference was observed in the metrics of systemic exposure or elimination of intravenous or oral midazolam or its major metabolite, 1’-hydroxymidazolam, between midazolam alone or together with rifaximin. Therefore, rifaximin was not shown to significantly affect intestinal or hepatic CYP3A4 activity for the 200 mg three times a day dosing regimen.

After XIFAXAN 550 mg was administered three times a day for 7 days and 14 days to healthy subjects, the mean AUC of single midazolam 2 mg orally was 3.8% and 8.8% lower, respectively, than when midazolam was administered alone. The mean Cmax of midazolam was also decreased by 4-5% when XIFAXAN was administered for 7-14 days prior to midazolam administration. This degree of interaction is not considered clinically meaningful.

The effect of rifaximin on CYP3A4 in patients with impaired liver function who have elevated systemic exposure is not known.

Oral Contraceptives Containing 0.07 mg Ethinyl Estradiol and 0.5 mg Norgestimate

The oral contraceptive study utilized an open-label, crossover design in 28 healthy female subjects to determine if rifaximin 200 mg orally administered three times a day for 3 days (the dosing regimen for travelers’ diarrhea) altered the pharmacokinetics of a single dose of an oral contraceptive containing 0.07 mg ethinyl estradiol and 0.5 mg norgestimate. Results showed that the pharmacokinetics of single doses of ethinyl estradiol and norgestimate were not altered by rifaximin [see Drug Interactions (7)].

Effect of rifaximin on oral contraceptives was not studied for XIFAXAN 550 mg twice a day, the dosing regimen for hepatic encephalopathy.

12.4 Microbiology

Mechanism of Action

Rifaximin is a non-aminoglycoside semi-synthetic antibacterial derived from rifamycin SV. Rifaximin acts by binding to the beta-subunit of bacterial DNA-dependent RNA polymerase resulting in inhibition of bacterial RNA synthesis.

Escherichia coli has been shown to develop resistance to rifaximin in vitro. However, the clinical significance of such an effect has not been studied.

Rifaximin is a structural analog of rifampin. Organisms with high rifaximin minimum inhibitory concentration (MIC) values also have elevated MIC values against rifampin. Cross-resistance between rifaximin and other classes of antimicrobials has not been studied.

Rifaximin has been shown to be active against the following pathogen in clinical studies of infectious diarrhea as described in the Indications and Usage (1) section: Escherichia coli (enterotoxigenic and enteroaggregative strains).

For HE, rifaximin is thought to have an effect on the gastrointestinal flora.

Susceptibility Tests

In vitro susceptibility testing was performed according to the National Committee for Clinical Laboratory Standards (NCCLS) agar dilution method M7-A6 [see References (15)]. However, the correlation between susceptibility testing and clinical outcome has not been determined.

13 NONCLINICAL TOXICOLOGY

13.1 Carcinogenesis, Mutagenesis, Impairment of Fertility

Malignant schwannomas in the heart were significantly increased in male Crl:CD® (SD) rats that received rifaximin by oral gavage for two years at 150 to 250 mg/kg/day (doses equivalent to 2.4 to 4 times the recommended dose of 200 mg three times daily for travelers’ diarrhea, and equivalent to 1.3 to 2.2 times the recommended dose of 550 mg twice daily for hepatic encephalopathy, based on relative body surface area comparisons). There was no increase in tumors in Tg.rasH2 mice dosed orally with rifaximin for 26 weeks at 150 to 2000 mg/kg/day (doses equivalent to 1.2 to 16 times the recommended daily dose for travelers’ diarrhea and equivalent to 0.7 to 9 times the recommended daily dose for hepatic encephalopathy, based on relative body surface area comparisons).

Rifaximin was not genotoxic in the bacterial reverse mutation assay, chromosomal aberration assay, rat bone marrow micronucleus assay, rat hepatocyte unscheduled DNA synthesis assay, or the CHO/HGPRT mutation assay. There was no effect on fertility in male or female rats following the administration of rifaximin at doses up to 300 mg/kg (approximately 5 times the clinical dose of 600 mg/day, and approximately 2.6 times the clinical dose of 1100 mg/day, adjusted for body surface area).

13.2 Animal Toxicology and/or Pharmacology

Oral administration of rifaximin for 3-6 months produced hepatic proliferation of connective tissue in rats (50 mg/kg/day) and fatty degeneration of liver in dogs (100 mg/kg/day). However, plasma drug levels were not measured in these studies. Subsequently, rifaximin was studied at doses as high as 300 mg/kg/day in rats for 6 months and 1000 mg/kg/day in dogs for 9 months, and no signs of hepatotoxicity were observed. The maximum plasma AUC0-8 hr values from the 6 month rat and 9 month dog toxicity studies (range: 42-127 ng•h/mL) was lower than the maximum plasma AUC0-8 hr values in cirrhotic patients (range: 19-306 ng•h/mL).

14 CLINICAL STUDIES

14.1 Travelers’ Diarrhea

The efficacy of XIFAXAN given as 200 mg orally taken three times a day for 3 days was evaluated in 2 randomized, multi‑center, double-blind, placebo-controlled studies in adult subjects with travelers’ diarrhea. One study was conducted at clinical sites in Mexico, Guatemala, and Kenya (Study 1). The other study was conducted in Mexico, Guatemala, Peru, and India (Study 2). Stool specimens were collected before treatment and 1 to 3 days following the end of treatment to identify enteric pathogens. The predominant pathogen in both studies was Escherichia coli.

The clinical efficacy of XIFAXAN was assessed by the time to return to normal, formed stools and resolution of symptoms. The primary efficacy endpoint was time to last unformed stool (TLUS) which was defined as the time to the last unformed stool passed, after which clinical cure was declared. Table 5 displays the median TLUS and the number of patients who achieved clinical cure for the intent to treat (ITT) population of Study 1. The duration of diarrhea was significantly shorter in patients treated with XIFAXAN than in the placebo group. More patients treated with XIFAXAN were classified as clinical cures than were those in the placebo group.

Table 5. Clinical Response in Study 1 (ITT population)
 | XIFAXAN (n=125) | Placebo (n=129) | Estimate (97.5% CI) | P-Value
Median TLUS (hours) | 32.5 | 58.6 | 1.78a; (1.26, 2.50) | 0.0002
Clinical cure, n (%) | 99 (79.2) | 78 (60.5) | 18.7b (5.3, 32.1) | 0.001
a Hazard Ratio
b Difference in rates

Microbiological eradication (defined as the absence of a baseline pathogen in culture of stool after 72 hours of therapy) rates for Study 1 are presented in Table 6 for patients with any pathogen at baseline and for the subset of patients with Escherichia coli at baseline. Escherichia coli was the only pathogen with sufficient numbers to allow comparisons between treatment groups.

Even though XIFAXAN had microbiologic activity similar to placebo, it demonstrated a clinically significant reduction in duration of diarrhea and a higher clinical cure rate than placebo. Therefore, patients should be managed based on clinical response to therapy rather than microbiologic response.

Table 6. Microbiologic Eradication Rates in Study 1 Subjects with a Baseline Pathogen
 | XIFAXAN | Placebo
Overall | 48/70 (68.6) | 41/61 (67.2)
E. coli | 38/53 (71.7) | 40/54 (74.1)

The results of Study 2 supported the results presented for Study 1. In addition, this study provided evidence that subjects treated with XIFAXAN with fever and/or blood in the stool at baseline had prolonged TLUS. These subjects had lower clinical cure rates than those without fever or blood in the stool at baseline. Many of the patients with fever and/or blood in the stool (dysentery-like diarrheal syndromes) had invasive pathogens, primarily Campylobacter jejuni, isolated in the baseline stool.

Also in this study, the majority of the subjects treated with XIFAXAN who had Campylobacter jejuni isolated as a sole pathogen at baseline failed treatment and the resulting clinical cure rate for these patients was 23.5% (4/17). In addition to not being different from placebo, the microbiologic eradication rates for subjects with Campylobacter jejuni isolated at baseline were much lower than the eradication rates seen for Escherichia coli.

In an unrelated open-label, pharmacokinetic study of oral XIFAXAN 200 mg taken every 8 hours for 3 days, 15 adult subjects were challenged with Shigella flexneri 2a, of whom 13 developed diarrhea or dysentery and were treated with XIFAXAN. Although this open-label challenge trial was not adequate to assess the effectiveness of XIFAXAN in the treatment of shigellosis, the following observations were noted: eight subjects received rescue treatment with ciprofloxacin either because of lack of response to XIFAXAN treatment within 24 hours (2), or because they developed severe dysentery (5), or because of recurrence of Shigella flexneri in the stool (1); five of the 13 subjects received ciprofloxacin although they did not have evidence of severe disease or relapse.

14.2 Hepatic Encephalopathy

The efficacy of XIFAXAN 550 mg taken orally two times a day was evaluated in a randomized, placebo-controlled, double-blind, multi-center 6-month trial of adult subjects from the U.S., Canada and Russia who were defined as being in remission (Conn score of 0 or 1) from hepatic encephalopathy (HE). Eligible subjects had ≥ 2 episodes of HE associated with chronic liver disease in the previous 6 months.

A total of 299 subjects were randomized to receive either XIFAXAN (n=140) or placebo (n=159) in this study. Patients had a mean age of 56 years (range, 21-82 years), 81% < 65 years of age, 61% were male and 86% White. At baseline, 67% of patients had a Conn score of 0 and 68% had an asterixis grade of 0. Patients had MELD scores of either ≤ 10 (27%) or 11 to 18 (64%) at baseline. No patients were enrolled with a MELD score of > 25. Nine percent of the patients were Child-Pugh Class C. Lactulose was concomitantly used by 91% of the patients in each treatment arm of the study. Per the study protocol, patients were withdrawn from the study after experiencing a breakthrough HE episode. Other reasons for early study discontinuation included: adverse reactions (XIFAXAN 6%; placebo 4%), patient request to withdraw (XIFAXAN 4%; placebo 6%) and other (XIFAXAN 7%; placebo 5%).

The primary endpoint was the time to first breakthrough overt HE episode. A breakthrough overt HE episode was defined as a marked deterioration in neurological function and an increase of Conn score to Grade ≥ 2. In patients with a baseline Conn score of 0, a breakthrough overt HE episode was defined as an increase in Conn score of 1 and asterixis grade of 1.

Breakthrough overt HE episodes were experienced by 31 of 140 subjects (22%) in the XIFAXAN group and by 73 of 159 subjects (46%) in the placebo group during the 6-month treatment period. Comparison of Kaplan-Meier estimates of event-free curves showed XIFAXAN significantly reduced the risk of HE breakthrough by 58% during the 6-month treatment period. Presented below in Figure 1 is the Kaplan-Meier event-free curve for all subjects (n = 299) in the study.

Figure 1: Kaplan-Meier Event-Free Curves^1 in HE Study (Time to First
Breakthrough-HE Episode up to 6 Months of Treatment, Day 170) (ITT
Population)

Note: Open diamonds and open triangles represent censored subjects.
^1Event-free refers to non-occurrence of breakthrough HE.

When the results were evaluated by the following demographic and baseline characteristics, the treatment effect of XIFAXAN 550 mg in reducing the risk of breakthrough overt HE recurrence was consistent for: sex, baseline Conn score, duration of current remission and diabetes. The differences in treatment effect could not be assessed in the following subpopulations due to small sample size: non-White (n=42), baseline MELD > 19 (n=26), Child-Pugh C (n=31), and those without concomitant lactulose use (n=26).

HE-related hospitalizations (hospitalizations directly resulting from HE, or hospitalizations complicated by HE) were reported for 19 of 140 subjects (14%) and 36 of 159 subjects (23%) in the XIFAXAN and placebo groups respectively. Comparison of Kaplan-Meier estimates of event-free curves showed XIFAXAN significantly reduced the risk of HE-related hospitalizations by 50% during the 6-month treatment period. Comparison of Kaplan-Meier estimates of event-free curves is shown in Figure 2.

Figure 2: Kaplan-Meier Event-Free Curves^1 in Pivotal HE Study (Time
to First HE-Related Hospitalization in HE Study up to 6 Months of
Treatment, Day 170) (ITT Population)

Note: Open diamonds and open triangles represent censored subjects.
^1Event-free refers to non-occurrence of HE-related hospitalization.

15 REFERENCES

Methods for dilution antimicrobial susceptibility tests for bacteria that grow aerobically. National Committee for Clinical Laboratory Standards, Sixth Edition, Wayne PA. Approved Standard NCCLS Document M7-A6 January 2003; 23 (2).

16 HOW SUPPLIED/STORAGE AND HANDLING

HOW SUPPLIED

200 mg tablet is a pink-colored, round, biconvex tablet with “Sx” debossed on one side. It is available in the following presentations:

- NDC 54868-5972-1, bottles of 03 tablets
- NDC 54868-5972-2, bottles of 09 tablets
- NDC 54868-5972-0, bottles of 30 tablets

The 550 mg tablet is a pink-colored, oval, biconvex tablet with “rfx” debossed on one side. It is available in the following presentations:

- NDC 54868-6154-0, bottles of 02 tablets
- NDC 54868-6154-1, bottles of 09 tablets
- NDC 54868-6154-2, bottles of 10 tablets

Storage

Store XIFAXAN Tablets at 20–25°C (68–77°F); excursions permitted to 15–30°C (59-86°F). See USP Controlled Room Temperature.

17 PATIENT COUNSELING INFORMATION

17.1 Persistent Diarrhea

For those patients being treated for travelers’ diarrhea, discontinue XIFAXAN if diarrhea persists more than 24-48 hours or worsens. Advise the patient to seek medical care for fever and/or blood in the stool [see Warnings and Precautions (5.1)].

17.2 Clostridium difficile-Associated Diarrhea

Clostridium difficile-associated diarrhea (CDAD) has been reported with use of nearly all antibacterial agents, including XIFAXAN, and may range in severity from mild diarrhea to fatal colitis. Treatment with antibiotics alters the normal flora of the colon which may lead to C. difficile. Patients can develop watery and bloody stools (with or without stomach cramps and fever) even as late as two or more months after having taken the last dose of the antibiotic. If diarrhea occurs after therapy or does not improve or worsens during therapy, advise patients to contact a physician as soon as possible [see Warnings and Precautions (5.4)].

17.3 Administration with Food

Inform patients that XIFAXAN may be taken with or without food.

17.4 Antibacterial Resistance

Counsel patients that antibacterial drugs including XIFAXAN should only be used to treat bacterial infections. They do not treat viral infections (e.g., the common cold). When XIFAXAN is prescribed to treat a bacterial infection, patients should be told that although it is common to feel better early in the course of therapy, the medication should be taken exactly as directed. Skipping doses or not completing the full course of therapy may (1) decrease the effectiveness of the immediate treatment and (2) increase the likelihood that bacteria will develop resistance and will not be treatable by XIFAXAN or other antibacterial drugs in the future.

17.5 Severe Hepatic Impairment

Patients should be informed that in patients with severe hepatic impairment (Child-Pugh C) there is an increase in systemic exposure to XIFAXAN [see Warnings and Precautions (5.4)].

Manufactured for:

Salix Pharmaceuticals, Inc.

Raleigh, NC 27615

XIFAXAN® is a trademark of Salix Pharmaceuticals, Inc., under license from Alfa Wassermann S.p.A.
Copyright © Salix Pharmaceuticals, Inc.

Rifaximin for Travelers' Diarrhea and Hepatic encephalopathy is protected by US Patent Nos. 7,045,620; 7,612,199; 7,902,206 and 7,906,542. Rifaximin for Travelers' Diarrhea is also protected by US Patent No. 7,928,115.

Web site: www.Salix.com

All rights reserved.

VENART-156-2

OCT 2011

Relabeling and Repackaging by:

Physicians Total Care, Inc.

Tulsa, Oklahoma 74146

PACKAGE LABEL – PRINCIPAL DISPLAY – XIFAXAN 200 mg Tablets

Xifaxan®
(rifaxamin) tablets 200 mg

Rx only

PACKAGE LABEL – PRINCIPAL DISPLAY – XIFAXAN 550 mg Tablets

Xifaxan®
(rifaximin) 550 mg tablets

Rx ONLY